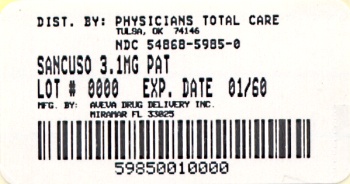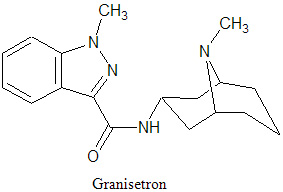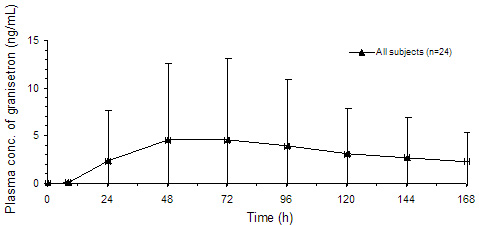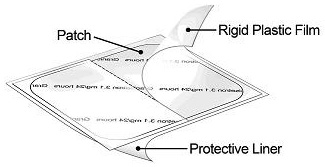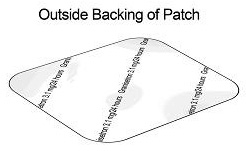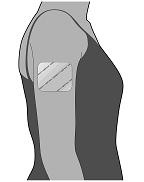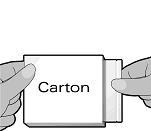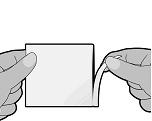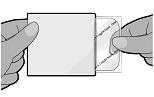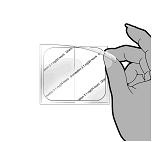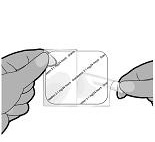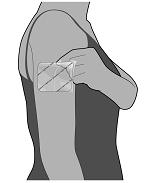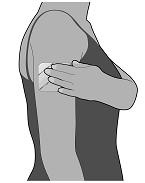 DRUG LABEL: Sancuso
NDC: 54868-5985 | Form: PATCH
Manufacturer: Physicians Total Care, Inc.
Category: prescription | Type: HUMAN PRESCRIPTION DRUG LABEL
Date: 20090930

ACTIVE INGREDIENTS: GRANISETRON 3.1 mg/24 h

HIGHLIGHTS OF PRESCRIBING INFORMATION

These highlights do not include all the information needed to use Sancuso (Granisetron Transdermal System) safely and effectively. See full prescribing information for Sancuso.
Sancuso (Granisetron Transdermal System)
Initial U.S. Approval: 2008

1 INDICATIONS AND USAGE

Sancuso is a serotonin subtype 3 (5-HT3) receptor antagonist indicated for the prevention of nausea and vomiting in patients receiving moderately and/or highly emetogenic chemotherapy for up to 5 consecutive days. (1)

2 DOSAGE AND ADMINISTRATION

Apply a single transdermal system (patch) to the upper outer arm a minimum of 24 hours before chemotherapy. The patch may be applied up to a maximum of 48 hours before chemotherapy as appropriate. Remove the patch a minimum of 24 hours after completion of chemotherapy. The patch can be worn for up to 7 days depending on the duration of the chemotherapy regimen. (2)

3 DOSAGE FORMS AND STRENGTHS

52 cm^2 patch containing 34.3 mg of granisetron delivering 3.1 mg per 24 hours (3)

4 CONTRAINDICATIONS

Known hypersensitivity to granisetron or to any of the components of the patch (4)

5 WARNINGS AND PRECAUTIONS

- Granisetron may mask a progressive ileus and/or gastric distention caused by the underlying condition. (5.1)
- Mild application site reactions have occurred; remove patch if severe reactions or a generalized skin reaction occur. (5.2)
- Avoid direct exposure of application site to natural or artificial sunlight by covering with clothing while wearing the patch and for 10 days after removing it. (5.3)

6 ADVERSE REACTIONS

The most common adverse reaction is constipation. (6)

To report SUSPECTED ADVERSE REACTIONS, contact ProStrakan Inc. at 1-800-SANCUSO and www.sancuso.com, or FDA at 1-800-FDA-1088 or www.fda.gov/medwatch.

7 DRUG INTERACTIONS

- No clinically relevant drug interactions have been reported in clinical studies with Sancuso. (7)

8 USE IN SPECIFIC POPULATIONS

- Use during pregnancy only if clearly needed. (8.1)
- Use caution when administering to nursing women. (8.3)
- Safety and effectiveness in pediatric patients have not been established. (8.4)
- Clinical studies of Sancuso did not include sufficient numbers of subjects aged 65 and over to determine whether they respond differently from younger patients (8.5)

FULL PRESCRIBING INFORMATION

1 INDICATIONS AND USAGE

Sancuso® (Granisetron Transdermal System) is indicated for the prevention of nausea and vomiting in patients receiving moderately and/or highly emetogenic chemotherapy regimens of up to 5 consecutive days duration.

2 DOSAGE AND ADMINISTRATION

The transdermal system (patch) should be applied to clean, dry, intact healthy skin on the upper outer arm. Sancuso should not be placed on skin that is red, irritated or damaged.

Each patch is packed in a pouch and should be applied directly after the pouch has been opened.

The patch should not be cut into pieces.

2.1 Adults

Apply a single patch to the upper outer arm a minimum of 24 hours before chemotherapy. The patch may be applied up to a maximum of 48 hours before chemotherapy as appropriate. Remove the patch a minimum of 24 hours after completion of chemotherapy. The patch can be worn for up to 7 days depending on the duration of the chemotherapy regimen.

3 DOSAGE FORMS AND STRENGTHS

Sancuso is a 52 cm^2 patch containing 34.3 mg of granisetron. The patch releases 3.1 mg of granisetron per 24 hours for up to 7 days.

4 CONTRAINDICATIONS

Sancuso is contraindicated in patients with known hypersensitivity to granisetron or to any of the components of the patch.

5 WARNINGS AND PRECAUTIONS

5.1 Gastrointestinal

The use of granisetron in patients may mask a progressive ileus and/or gastric distention caused by the underlying condition.

5.2 Skin Reactions

In clinical trials with Sancuso, application site reactions were reported which were generally mild in intensity and did not lead to discontinuation of use. The incidence of reactions was comparable with placebo.

If severe reactions, or a generalized skin reaction occur (e.g. allergic rash, including erythematous, macular, papular rash or pruritus), the patch must be removed.

5.3 Exposure to Sunlight

Granisetron may be affected by direct natural or artificial sunlight. Patients must be advised to cover the patch application site, e.g. with clothing, if there is a risk of exposure to sunlight throughout the period of wear and for 10 days following its removal because of a potential skin reaction (see Section 13.2).

6 ADVERSE REACTIONS

6.1 Clinical Trials Experience

The safety of Sancuso was evaluated in a total of 404 patients undergoing chemotherapy who participated in two double-blind, comparator studies with patch treatment durations of up to 7 days. The control groups included a total of 406 patients who received a daily dose of 2 mg oral granisetron, for 1 to 5 days.

Adverse reactions considered by the investigators as drug-related occurred in 8.7% (35/404) of patients receiving Sancuso and 7.1% (29/406) of patients receiving oral granisetron. The most common adverse reaction was constipation that occurred in 5.4% of patients in the Sancuso group and 3.0% of patients in the oral granisetron group.

Table 1 lists the treatment emergent adverse reactions that occurred in at least 3% of patients treated with Sancuso or oral granisetron.

Table 1: Incidence of Adverse Reactions in Double-Blind, Active Comparator Controlled Studies in Cancer Patients Receiving Chemotherapy (Events ≥ 3% in either group)
Body System Preferred Term | Sancuso TDS N=404 (%) | Oral granisetron N=406 (%)
Gastrointestinal disorders
Constipation | 5.4 | 3.0
Nervous system disorders
Headache | 0.7 | 3.0

5-HT3 receptor antagonists, such as granisetron, may be associated with arrhythmias or ECG abnormalities. Three ECGs were performed on 588 randomized patients in the Phase 3 study: at baseline before treatment, the first day of chemotherapy, and 5 to 7 days after starting chemotherapy. QTcF prolongation greater than 450 milliseconds was seen in a total of 11 (1.9%) patients after receiving granisetron, 8 (2.7%) on oral granisetron and 3 (1.1%) on the patch. No new QTcF prolongation greater than 480 milliseconds was observed in any patient in this study. No arrhythmias were detected in this study.

6.2 Granisetron Experience

Because clinical trials are conducted under widely varying conditions, adverse reaction rates observed in the clinical trials of a drug cannot be directly compared to rates in the clinical trials of another drug and may not reflect the rates observed in practice.

Adverse events reported in clinical trials with other formulations of granisetron include the following:

Gastrointestinal: abdominal pain, diarrhea, constipation, elevation of ALT and AST levels, nausea and vomiting

Cardiovascular: Hypertension, hypotension, angina pectoris, atrial fibrillation and syncope have been observed rarely

Central Nervous System: dizziness, insomnia, headache, anxiety, somnolence and asthenia

Hypersensitivity: rare cases of hypersensitivity reactions, sometimes severe (e.g. anaphylaxis, shortness of breath, hypotension, urticaria) have been reported

Other: fever; events often associated with chemotherapy have also been reported: leucopenia, decreased appetite, anemia, alopecia, thrombocytopenia.

7 DRUG INTERACTIONS

Granisetron does not induce or inhibit the cytochrome P-450 drug-metabolizing enzyme system in vitro. There have been no definitive drug-drug interaction studies to examine pharmacokinetic or pharmacodynamic interaction with other drugs. However, in humans, granisetron hydrochloride injection has been safely administered with drugs representing benzodiazepines, neuroleptics and anti-ulcer medications commonly prescribed with antiemetic treatments. Granisetron hydrochloride injection also does not appear to interact with emetogenic cancer therapies. In agreement with these data, no clinically relevant drug interactions have been reported in clinical studies with Sancuso.

Because granisetron is metabolized by hepatic cytochrome P-450 drug-metabolizing enzymes (CYP1A1 and CYP3A4), inducers or inhibitors of these enzymes may change the clearance and hence, the half-life of granisetron. In addition, the activity of the cytochrome P-450 subfamily 3A4 (involved in the metabolism of some of the main narcotic analgesic agents) is not modified by granisetron hydrochloride in vitro. In in vitro human microsomal studies, ketoconazole inhibited ring oxidation of granisetron hydrochloride. However, the clinical significance of in vivo pharmacokinetic interactions with ketoconazole is not known. In a human pharmacokinetic study, hepatic enzyme induction with phenobarbital resulted in a 25% increase in total plasma clearance of intravenous granisetron hydrochloride. The clinical significance of this change is not known.

8 USE IN SPECIFIC POPULATIONS

8.1 Pregnancy

Pregnancy Category B

Reproduction studies with granisetron hydrochloride have been performed in pregnant rats at intravenous doses up to 9 mg/kg/day (54 mg/m^2/day, about 24 times the recommended human dose delivered by the Sancuso patch, based on body surface area) and oral doses up to 125 mg/kg/day (750 mg/m^2/day, about 326 times the recommended human dose with Sancuso based on body surface area). Reproduction studies have been performed in pregnant rabbits at intravenous doses up to 3 mg/kg/day (36 mg/m^2/day, about 16 times the human dose with Sancuso based on body surface area) and at oral doses up to 32 mg/kg/day (384 mg/m^2/day, about 167 times the human dose with Sancuso based on body surface area). These studies did not reveal any evidence of impaired fertility or harm to the fetus due to granisetron. There are, however, no adequate and well-controlled studies in pregnant women. Because animal reproduction studies are not always predictive of human response, Sancuso should be used during pregnancy only if clearly needed.

8.3 Nursing Mothers

It is not known whether granisetron is excreted in human milk. Because many drugs are excreted in human milk, caution should be exercised when Sancuso is administered to a nursing woman.

8.4 Pediatric Use

Safety and effectiveness of Sancuso in pediatric patients under 18 years of age have not been established.

8.5 Geriatric Use

Clinical studies of Sancuso did not include sufficient numbers of subjects aged 65 and over to determine whether they respond differently from younger subjects. Other reported clinical experience has not identified differences in responses between the elderly and younger patients. In general, cautious treatment selection for an elderly patient is prudent because of the greater frequency of decreased hepatic, renal, or cardiac function, and of concomitant disease or other drug therapy.

8.6 Renal Failure or Hepatically-Impaired Patients

Although no studies have been performed to investigate the pharmacokinetics of Sancuso in patients with renal or hepatic impairment, pharmacokinetic information is available for intravenous granisetron (see CLINICAL PHARMACOLOGY: Pharmacokinetics 12.3).

10 OVERDOSAGE

There is no specific antidote for granisetron overdosage. In the case of overdosage, symptomatic treatment should be given.

Overdosage of up to 38.5 mg of granisetron hydrochloride, as a single intravenous injection, has been reported without symptoms or only the occurrence of a slight headache.

In clinical trials there were no reported cases of overdosage with Sancuso.

11 DESCRIPTION

Sancuso contains granisetron, which is an anti-nauseant and antiemetic agent. Chemically it is 1-methyl-N-[(1R,3r,5S)-9-methyl-9-azabicyclo[3.3.1]non-3-yl]-1H-indazole-3-carboxamide with a molecular weight of 312.4. Its empirical formula is C18H24N4O, while its chemical structure is:

Granisetron is a white to off-white solid that is insoluble in water. Sancuso is a thin, translucent, matrix-type transdermal patch that is rectangular-shaped with rounded corners, consisting of a backing, the drug matrix and a release liner.

12 CLINICAL PHARMACOLOGY

12.1 Mechanism of Action

Granisetron is a selective 5-hydroxytryptamine3 (5-HT3) receptor antagonist with little or no affinity for other serotonin receptors, including 5-HT1, 5-HT1A, 5-HT1B/C, 5-HT2; for alpha1-, alpha2-, or beta-adrenoreceptors; for dopamine-D2; or for histamine-H1; benzodiazepine; picrotoxin or opioid receptors.

Serotonin receptors of the 5-HT3 type are located peripherally on vagal nerve terminals and centrally in the chemoreceptor trigger zone of the area postrema. During chemotherapy that induces vomiting, mucosal enterochromaffin cells release serotonin, which stimulates 5-HT3 receptors. This evokes vagal afferent discharge, inducing vomiting. Animal studies demonstrate that, in binding to 5-HT3 receptors, granisetron blocks serotonin stimulation and subsequent vomiting after emetogenic stimuli such as cisplatin. In the ferret animal model, a single granisetron injection prevented vomiting due to high-dose cisplatin or arrested vomiting within 5 to 30 seconds.

12.2 Pharmacodynamics

The effect of granisetron on QTc prolongation was evaluated in a randomized, single-blind, positive (moxifloxacin 400 mg) - and placebo controlled parallel study in healthy subjects. A total of 240 subjects were administered Sancuso patch, intravenous granisetron (10 mcg/kg over 30 seconds). In a study with demonstrated ability to detect small effects, the upper bound of the 90% confidence interval for the largest placebo adjusted, baseline corrected QTc based on Fridericia correction method (QTcF) for Sancuso was below 10 ms, the threshold for regulatory concern.

No evidence of an effect on plasma prolactin or aldosterone concentrations has been found in studies using granisetron.

The effect on oro-cecal transit time following application of Sancuso has not been studied. Granisetron hydrochloride injection exhibited no effect on oro-cecal transit time in healthy subjects given a single intravenous infusion of 50 mcg/kg or 200 mcg/kg. Single and multiple oral doses of granisetron hydrochloride slowed colonic transit in healthy subjects.

12.3 Pharmacokinetics

Absorption

Granisetron crosses intact skin into the systemic circulation by a passive diffusion process.

Following a 7-day application of Sancuso in 24 healthy subjects, high inter-subject variability in systemic exposure was observed. Maximal concentration was reached at approximately 48 hours (range: 24-168 hours) following patch application. Mean Cmax was 5.0 ng/mL (CV: 170%) and mean AUC0-168hr was 527 ng-hr/mL (CV:173%).

Mean Plasma Concentration of Granisetron (mean ± SD)

Based on the measure of residual content of the patch after removal, approximately 66% (SD: ± 10.9) of granisetron is delivered following patch application for 7 days.

Distribution

Plasma protein binding is approximately 65%. Granisetron distributes freely between plasma and red blood cells.

Metabolism

Granisetron metabolism involves N-demethylation and aromatic ring oxidation followed by conjugation. In vitro liver microsomal studies show that granisetron's major route of metabolism is inhibited by ketoconazole, suggestive of metabolism mediated by the cytochrome P-450 3A subfamily. Animal studies suggest that some of the metabolites may also have 5-HT3 receptor antagonist activity.

Elimination

Clearance is predominantly by hepatic metabolism. Based on a study with intravenous injection, approximately 12% of the dose is excreted unchanged in the urine of healthy subjects in 48 hours. The remainder of the dose is excreted as metabolites, 49% in the urine, and 34% in the feces.

Subpopulations

Gender

There is evidence to suggest that female subjects had higher granisetron concentrations than males following patch application. However, no statistically significant difference in clinical efficacy outcome was observed between genders.

Pediatrics

No studies have been performed to investigate the pharmacokinetics of Sancuso in pediatrics.

Elderly, and Renal or Hepatic Impairment

Although no studies have been performed to investigate the pharmacokinetics of Sancuso in elderly subjects, and in patients with renal or hepatic impairment, the following pharmacokinetic information is available for intravenous granisetron.

In the elderly, and in patients with renal failure or hepatic impairment, the pharmacokinetics of granisetron were determined following a single 40 mcg/kg intravenous dose of granisetron hydrochloride.

Elderly

In elderly volunteers (mean age 71 years) pharmacokinetic parameters following a single 40 mcg/kg intravenous dose of granisetron hydrochloride, lower clearance and longer half-life were observed compared to younger healthy volunteers.

Renal Failure Patients

Total clearance of granisetron was not affected in patients with severe renal failure who received a single 40 mcg/kg intravenous dose of granisetron hydrochloride.

Hepatically-Impaired Patients

In patients with hepatic impairment due to neoplastic liver involvement, total plasma clearance following a single 40 mcg/kg intravenous dose of granisetron hydrochloride was approximately halved compared to patients without hepatic impairment. Given the wide variability in pharmacokinetic parameters of granisetron and the good tolerance of doses well above the recommended dose, dose adjustment in patients with hepatic functional impairment is not necessary.

13 NONCLINICAL TOXICOLOGY

13.1 Carcinogenesis, Mutagenesis and Impairment of Fertility

In a 24-month carcinogenicity study, rats were treated orally with granisetron 1, 5 or 50 mg/kg/day (6, 30 or 300 mg/m^2/day). The 50 mg/kg/day dose was reduced to 25 mg/kg/day (150 mg/m^2/day) during week 59 due to toxicity. For a 50 kg person of average height (1.46 m^2 body surface area), these doses represent about 2.6, 13 and 65 times the recommended clinical dose (3.1 mg/day, 2.3 mg/m^2/day, delivered by the Sancuso patch, on a body surface area basis). There was a statistically significant increase in the incidence of hepatocellular carcinomas and adenomas in males treated with 5 mg/kg/day (30 mg/m^2/day, about 13 times the recommended human dose with Sancuso, on a body surface area basis) and above, and in females treated with 25 mg/kg/day (150 mg/m^2/day, about 65 times the recommended human dose with Sancuso, on a body surface area basis). No increase in liver tumors was observed at a dose of 1 mg/kg/day (6 mg/m^2/day, about 2.6 times the recommended human dose with Sancuso, on a body surface area basis) in males and 5 mg/kg/day (30 mg/m^2/day, about 13 times the recommended human dose with Sancuso, on a body surface area basis) in females.

In a 12-month oral toxicity study, treatment with granisetron 100 mg/kg/day (600 mg/m^2/day, about 261 times the recommended human dose with Sancuso, on a body surface area basis) produced hepatocellular adenomas in male and female rats while no such tumors were found in the control rats. A 24-month mouse carcinogenicity study of granisetron did not show a statistically significant increase in tumor incidence, but the study was not conclusive.

Because of the tumor findings in rat studies, Sancuso should be prescribed only at the dose and for the indication recommended (see INDICATIONS AND USAGE, and DOSAGE AND ADMINISTRATION).

Granisetron was not mutagenic in an in vitro Ames test and mouse lymphoma cell forward mutation assay, and in vivo mouse micronucleus test and in vitro and ex vivo rat hepatocyte UDS assays. It, however, produced a significant increase in UDS in HeLa cells in vitro and a significant increased incidence of cells with polyploidy in an in vitro human lymphocyte chromosomal aberration test.

Granisetron at subcutaneous doses up to 6 mg/kg/day (36 mg/m^2/day, about 16 times the recommended human dose of Sancuso, on a body surface area basis), and oral doses up to 100 mg/kg/day (600 mg/m^2/day, about 261 times the recommended human dose of Sancuso, on a body surface area basis) was found to have no effect on fertility and reproductive performance of male and female rats.

13.2 Phototoxicity

When tested for potential photogenotoxicity in vitro in a Chinese hamster ovary (CHO) cell line, at 200 and 300 mcg/ml, granisetron increased the percentage of cells with chromosomal aberration following photoirradiation.

Granisetron was not phototoxic when tested in vitro in a mouse fibroblast cell line. When tested in vivo in guinea-pigs, Sancuso patches did not show any potential for photoirritation or photosensitivity. No phototoxicity studies have been performed in humans.

14 CLINICAL STUDIES

The effectiveness of Sancuso in the prevention of chemotherapy-induced nausea and vomiting (CINV) was evaluated in a Phase 3 randomized, parallel group, double-blind, double-dummy study conducted in the U.S. and abroad. The study compared the efficacy, tolerability and safety of Sancuso with that of 2 mg oral granisetron once daily in the prevention of nausea and vomiting in a total of 641 patients receiving multi-day chemotherapy.

The population randomized into the trial included 48% males and 52% females aged 16 to 86 years receiving moderately (ME) or highly emetogenic (HE) multi-day chemotherapy. Seventy-eight (78%) of patients were White, 12% Asian, 10% Hispanic/Latino and 0% Black.

The granisetron patch was applied 24 to 48 hours before the first dose of chemotherapy, and kept in place for 7 days. Oral granisetron was administered daily for the duration of the chemotherapy regimen, one hour before each dose of chemotherapy. Efficacy was assessed from the first administration until 24 hours after the start of the last day's administration of the chemotherapy regimen.

The primary endpoint of the trial was the proportion of patients achieving no vomiting and/or retching, no more than mild nausea and no rescue medication from the first administration until 24 hours after the start of the last day's administration of multi-day chemotherapy. Using this definition, the effect of Sancuso was established in 60.2% of patients in the Sancuso arm and 64.8% of patients receiving oral granisetron (difference -4.89%; 95% confidence interval -12.91% to +3.13%).

An assessment of patch adhesion in 621 patients receiving either active or placebo patches showed that less than 1% of patches became detached over the course of the 7 day period of patch application.

16 HOW SUPPLIED/STORAGE AND HANDLING

Sancuso (Granisetron Transdermal System) is supplied as a 52 cm^2 patch containing 34.3 mg of granisetron. Each patch is printed on one side with the words "Granisetron 3.1 mg/24 hours". Each patch is packaged in a separate sealed foil-lined plastic pouch.

Sancuso is available in packages of 1 (NDC 54868-5985-0) patch.

Store at 20°-25°C (68°-77°F); excursions permitted between 15°-30°C (59°-86°F). [see USP Controlled Room Temperature].

Sancuso should be stored in the original packaging.

17 PATIENT COUNSELING INFORMATION

See FDA-approved patient labeling (17.4)

17.1 Gastrointestinal

Because the use of granisetron may mask a progressive ileus and/or gastric distention caused by the underlying condition, patients should be instructed to tell their physician if they have pain or swelling in their abdomen.

17.2 Skin Reactions

Patients should be instructed to remove the patch if they have a severe skin reaction, or a generalized skin reaction (e.g. allergic rash, including erythematous, macular, papular rash or pruritus).

When patients remove the patch, they should be instructed to peel it off gently.

17.3 Exposure to Sunlight

Granisetron may be degraded by direct sunlight or exposure to sunlamps. In addition, an in vitro study using Chinese hamster ovary cells suggests that granisetron has the potential for photogenotoxicity (see Section 13.2).

Patients must be advised to cover the patch application site, e.g. with clothing, if there is a risk of exposure to sunlight or sunlamps throughout the period of wear and for 10 days following its removal.

17.4 FDA-Approved Patient Labeling

Rx Only

Manufactured by:

Aveva Drug Delivery Systems Inc.,
Miramar
FL 33025

Manufactured for:

ProStrakan Inc.,
Bedminster
NJ 07921

Copyright © 2008, ProStrakan Inc. All rights reserved.

Sancuso and ProStrakan are trademarks owned by the ProStrakan group of companies

Revised: September 2011

Additional barcode label applied by:
Physicians Total Care, Inc.
Tulsa, OK 74146

Patient Information

Sancuso® [san-KOO-so]
(granisetron transdermal system)

IMPORTANT: For skin use only

Read the Patient Information that comes with Sancuso before you start using it and each time you get a refill. There may be new information. This information does not take the place of talking to your healthcare provider about your medical condition or your treatment. If you have any questions about Sancuso, ask your healthcare provider.

What is Sancuso?

Sancuso is a prescription medicine used to prevent nausea and vomiting in people receiving some types of chemotherapy treatment. Sancuso is a skin patch that slowly releases the medicine contained in the adhesive (glue), through clean and intact skin areas into your bloodstream while you wear the patch.

Important: Sancuso contains granisetron, the same medicine in Kytril. Do not take Kytril at the same time you use Sancuso unless your healthcare provider tells you it is alright.

Who should not use Sancuso?

Do not use Sancuso if you are allergic to any of the ingredients in Sancuso. See the end of this leaflet for a list of ingredients in Sancuso.

What should I tell my healthcare provider before using Sancuso?

Tell your healthcare provider about all your medical conditions, including if you:

- are allergic to medical adhesive tape, adhesive dressings or other skin patches.
- have pain or swelling in your stomach area (abdomen).
- are pregnant. It is not known if Sancuso will harm your unborn baby. Talk to your healthcare provider if you are pregnant or plan to become pregnant.
- are breast-feeding or plan to breast-feed. It is not known if Sancuso passes into your breast milk.

Tell your healthcare provider about all the medicines you take, including prescription and non-prescription medicines, vitamins and herbal supplements. Other medicines may affect how Sancuso works. Sancuso may also affect how other medicines work.

How should Sancuso be used?

Use Sancuso exactly as prescribed. See the detailed Patient Instructions for Applying Sancuso at the end of this Patient Information leaflet.

Avoid sunlight. The medicine in Sancuso (granisetron) may not work as well and/or may affect your skin if exposed to direct sunlight or the light from sunlamps or tanning beds. It is important to do the following:

- While you wear the patch, keep it covered with clothing if you will be in sunlight or near a sunlamp, including tanning beds.
- Keep the skin where Sancuso was applied covered for another 10 days after the patch is taken off to protect from exposure to direct sunlight.

What are the possible side effects of Sancuso?

Sancuso can cause serious side effects:

- Using Sancuso may make it harder to identify certain stomach and bowel problems that are from other causes. Tell your healthcare provider if you have any stomach area (abdominal) pain or swelling while using Sancuso.
- Skin reactions. Skin reactions can happen just at the patch application site or outside the patch application site. Tell your healthcare provider if you get any redness, rashes, bumps, blisters or itching at the patch application site, and especially if they spread outside the place where the patch was or if they appear outside the patch application site. You may need to stop using Sancuso.

Common side effects of Sancuso are:

- constipation
- headache.

Tell your healthcare provider if you have any side effect that bothers you or that does not go away. These are not all the possible side effects of Sancuso. For more information, ask your healthcare provider or pharmacist.

Call your doctor for medical advice about side effects. You may report side effects to FDA at 1-800-FDA-1088.

How should I store Sancuso?

- Keep Sancuso in the package it comes in.
- Store Sancuso at 20-25°C (68-77°F).

Keep Sancuso out of the reach of children.

General information about Sancuso

Medicines are sometimes prescribed for conditions that are not mentioned in Patient Information leaflets. Do not use Sancuso for a condition for which it is not prescribed. Do not give Sancuso to other people, even if they have the same symptoms you have. It may harm them.

This Patient Information leaflet summarizes the most important information about Sancuso. If you would like more information, talk to your healthcare provider. You can ask your pharmacist or healthcare provider for information about Sancuso that is written for health professionals.

For more information, go to www.sancuso.com or call 1-800-SANCUSO.

Patient Instructions for Applying Sancuso

When do I apply the Sancuso patch?

- Apply Sancuso at least 1 day (24 hours) before your scheduled chemotherapy treatment.
- You may apply Sancuso up to 2 days (48 hours) before your scheduled chemotherapy.
- Wear the patch all the time during your chemotherapy.
- Sancuso may be worn for up to 7 days, depending on how long your chemotherapy treatment lasts (up to 5 days).
- Remove the patch at least 1 day (24 hours) after your chemotherapy is finished.
- Keep the patch covered, such as under clothing, while you are wearing it to avoid a skin reaction to sunlight or sunlamps. Keep the skin where Sancuso was applied (application site) covered up for another 10 days after the patch is taken off to prevent a skin reaction. See "What should I avoid while using Sancuso?"

Where do I apply the Sancuso patch?

- Apply Sancuso to a clean, dry, healthy area of skin on the outside part of your upper arm.
- The area you choose should not be oily, recently shaved or have any skin problems such as being damaged (cut or scraped) or irritated (redness or a rash).
- Do not apply Sancuso to areas that have been treated with creams, oils, lotions, powders or other skin products that could keep the patch from sticking well to your skin.

How do I apply the Sancuso patch?

The Sancuso patch comes inside a pouch which is inside the carton.

1. Do not remove the patch from the pouch until you are ready to use it.
2. Do not cut the Sancuso patch into pieces.
3. Remove the pouch from the carton.
4. Tear the pouch open using the slit provided, and remove the patch. Each pouch contains one Sancuso patch stuck onto a rigid plastic film, and a separate thin, clear protective liner.
5. Remove the thin, clear protective liner to expose the printed side of the patch. Throw away the liner. The protective liner is only included in the pouch to separate the patch from the inside of the pouch, and is not part of the patch.
6. The unprinted, sticky side of the patch is covered by a two-piece rigid plastic film. Bend the patch in the middle and remove one half of the rigid plastic film. Be careful not to stick the patch to itself and avoid touching the sticky side of the patch.
7. While holding the remaining half of the rigid plastic film, apply the patch to your skin. Remove the second half of the rigid plastic film and press the whole patch firmly in place with your fingers and smooth down. Press firmly making sure it sticks well to the skin, especially around the edges.
8. Wash your hands right away after applying the patch to remove any medicine that may have stuck to your fingers.
9. Keep the patch in place for the whole time you are having chemotherapy. Remove the patch at least 1 day (24 hours) after your chemotherapy is finished. The patch can be worn for up to 7 days, depending on the number of days your chemotherapy treatment lasts.
10. Do not re-use the patch after you remove it. See below for instructions on the right way to remove and throw away the patch.

What to do if the Sancuso patch does not stick well?

If the patch does not stick well, you may use surgical bandages or medical adhesive tape to keep the patch in place. Place tape or bandages on the edges of the patch. Do not completely cover the patch with bandages or tape and do not wrap completely around your arm. If the patch comes more than half off or it becomes damaged see your healthcare provider.

Can I bathe or shower while wearing Sancuso?

You can continue to shower and wash normally while wearing the Sancuso patch. It is not known how other activities, for example swimming, strenuous exercise or using a sauna or whirlpool, may affect Sancuso. Avoid these activities while wearing Sancuso.

How do I remove and dispose of Sancuso?

1. When you remove the patch, peel it off gently.
2. The used patch will still contain some of the medicine. After removing the used Sancuso patch, fold it in half so that the sticky side sticks to itself. Throw away the Sancuso patch in the garbage, out of the reach of children and pets. Do not re-use the patch.
3. After removing the patch you may find some adhesive is left on your skin. Gently wash the area with soap and water to remove it. Do not use alcohol or other dissolving liquids, such as nail polish remover. These may cause skin irritation.
4. Wash your hands after handling the patch.
5. You may see mild redness on the skin where the patch is removed. This redness should go away within three days. If redness continues, tell your healthcare provider.

What are the ingredients in Sancuso?

Active ingredient: granisetron.

Inactive ingredients: acrylate-vinylacetate copolymer, polyester, titanium dioxide, polyamide resin and polyethylene wax.

Manufactured by:
Aveva Drug Delivery Systems Inc., Miramar, FL 33025

Manufactured for:
ProStrakan Inc., Bedminster, NJ 07921

Copyright © 2008 ProStrakan Inc. All rights reserved.

Sancuso and ProStrakan are trademarks owned by the ProStrakan group of companies

Revised: 07/2008

PACKAGE LABEL

PRINCIPAL DISPLAY PANEL

NDC 54868-5985-0

Sancuso®
(Granisetron Transdermal System)
3.1 mg/24 hours

Rx Only

7 day patch
Each 52 cm^2 patch contains 34.3 mg of granisetron in an acrylate-vinylacetate copolymer adhesive

1 patch

www.sancuso.com